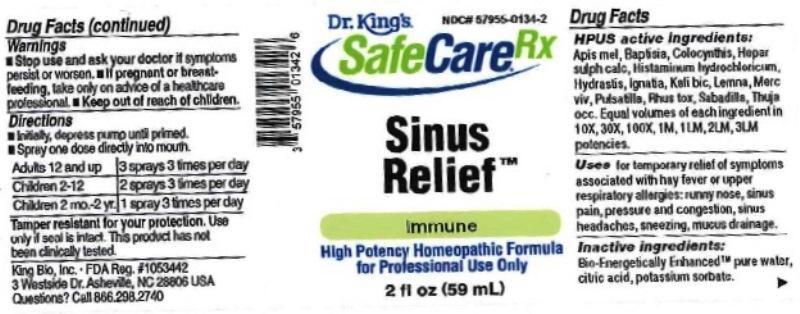 DRUG LABEL: Sinus Relief
NDC: 57955-0134 | Form: LIQUID
Manufacturer: King Bio Inc.
Category: homeopathic | Type: HUMAN OTC DRUG LABEL
Date: 20161214

ACTIVE INGREDIENTS: APIS MELLIFERA 10 [hp_X]/59 mL; BAPTISIA TINCTORIA ROOT 10 [hp_X]/59 mL; CITRULLUS COLOCYNTHIS FRUIT PULP 10 [hp_X]/59 mL; CALCIUM SULFIDE 10 [hp_X]/59 mL; HISTAMINE DIHYDROCHLORIDE 10 [hp_X]/59 mL; GOLDENSEAL 10 [hp_X]/59 mL; STRYCHNOS IGNATII SEED 10 [hp_X]/59 mL; POTASSIUM DICHROMATE 10 [hp_X]/59 mL; LEMNA MINOR 10 [hp_X]/59 mL; MERCURY 10 [hp_X]/59 mL; PULSATILLA VULGARIS 10 [hp_X]/59 mL; TOXICODENDRON PUBESCENS LEAF 10 [hp_X]/59 mL; SCHOENOCAULON OFFICINALE SEED 10 [hp_X]/59 mL; THUJA OCCIDENTALIS LEAFY TWIG 10 [hp_X]/59 mL
INACTIVE INGREDIENTS: WATER; ANHYDROUS CITRIC ACID; POTASSIUM SORBATE

Sinus Relief

Drug Facts

____________________________________________________________________________________________________________________

HPUS active ingredients: Apis mellifica, Baptisia tinctoria, Colocynthis, Hepar sulphuris calcareum, Histaminum hydrochloricum, Hydrastis canadensis, Ignatia amara, Kali bichromicum, Lemna minor, Mercurius vivus, Pulsatilla, Rhus toxicodendron, Sabadilla, Thuja occidentalis. Equal volumes of each ingredient in 10X, 30X, 100X, 1M, 1LM, 2LM, 3LM potencies.

INDICATIONS AND USAGE

Uses for temporary relief of symptoms associated with hay fever or upper respiratory allergies: runny nose, sinus pain, pressure and congestion, sinus headaches, sneezing, mucus drainage.

INACTIVE INGREDIENT

Inactive ingredients: Bio-Energetically Enhanced pure water, citric acid, potassium sorbate.

Warnings

- Stop use and ask your doctor if symptoms persist or worsen.
- If pregnant or breast-feeding, take only on advice of a healthcare professional.

- Keep out of reach of children.

Directions:

- Initially, depress pump until primed.
- Spray one dose directly into mouth.
- Adults: 3 sprays 3 times per day.
- Children (2-12 years): 2 sprays 3 times per day.
- Children (1 month-2 years): 1 spray 3 times per day.

OTHER SAFETY INFORMATION

Tamper resistant for your protection. Use only if safety seal is intact. This product has not been clinically tested.

PURPOSE

Uses for temporary relief of symptoms associated with hay fever or upper respiratory allergies:

- runny nose
- sinus pain
- pressure and congestion
- sinus headaches
- sneezing
- mucus drainage